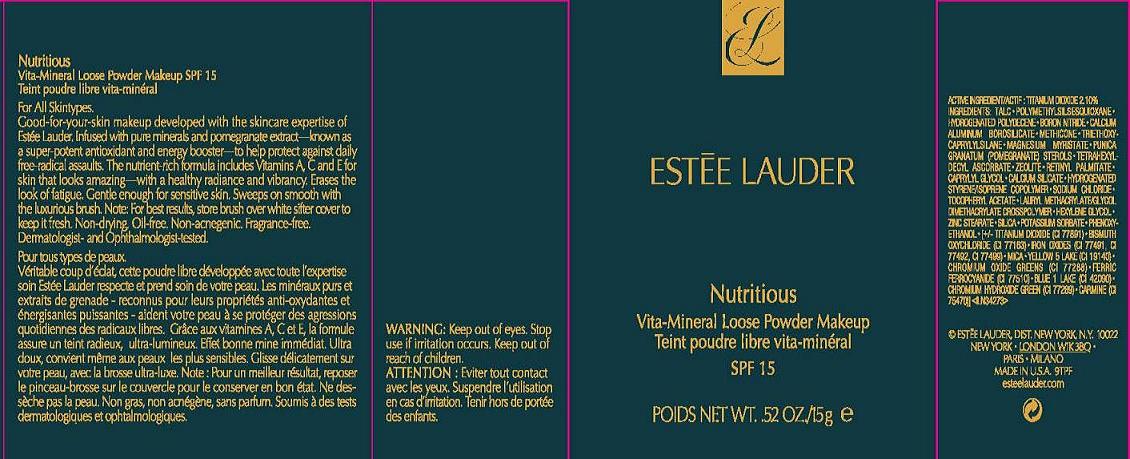 DRUG LABEL: NUTRITIOUS
NDC: 11559-727 | Form: POWDER
Manufacturer: ESTEE LAUDER INC
Category: otc | Type: HUMAN OTC DRUG LABEL
Date: 20110627

ACTIVE INGREDIENTS: TITANIUM DIOXIDE 2.1 g/100 g
INACTIVE INGREDIENTS: HYDROGENATED POLYDECENE (550 MW); TALC; POLYMETHYLSILSESQUIOXANE (11 MICRONS); BORON NITRIDE; DIMETHICONE; TRIETHOXYCAPRYLYLSILANE; MAGNESIUM MYRISTATE; TETRAHEXYLDECYL ASCORBATE; CAPRYLYL GLYCOL; CALCIUM SILICATE; SODIUM CHLORIDE; ALPHA-TOCOPHEROL ACETATE; HEXYLENE GLYCOL; ZINC STEARATE; SILICON DIOXIDE; POTASSIUM SORBATE; PHENOXYETHANOL; FERRIC OXIDE RED; BISMUTH OXYCHLORIDE; MICA; FD&C YELLOW NO. 5; FERRIC FERROCYANIDE; FD&C BLUE NO. 1; CHROMIC OXIDE; COCHINEAL

ACTIVE INGREDIENT: TITANIUM DIOXIDE 2.10%

INACTIVE INGREDIENT

INACTIVE INGREDIENTS: TALC [] POLYMETHYLSILSESQUIOXANE [] HYDROGENATED POLYDECENE [] BORON NITRIDE [] CALCIUM ALUMINUM BOROSILICATE [] METHICONE [] TRIETHOXYCAPRYLYLSILANE [] MAGNESIUM MYRISTATE [] PHYTOSTEROLS [] TETRAHEXYLDECYL ASCORBATE [] ZEOLITE [] CAPRYLYL GLYCOL [] CALCIUM SILICATE [] HYDROGENATED STYRENE/ ISOPRENE COPOLYMER [] SODIUM CHLORIDE [] TOCOPHERYL ACETATE [] LAURYL METHACRYLATE/GLYCOL DIMETHACRYLATE CROSSPOLYMER [] HEXYLENE GLYCOL [] ZINC STEARATE [] SILICA [] POTASSIUM SORBATE [] PHENOXYETHANOL [] [+/- TITANIUM DIOXIDE (CI 77891) [] BISMUTH OXYCHLORIDE (CI 77163) [] IRON OXIDES (CI 77491, CI 77492, CI 77499) [] MICA [] YELLOW 5 LAKE (CI 19140) [] FERRIC FERROCYANIDE (CI 77510) [] BLUE 1 LAKE (CI 42090) [] CHROMIUM OXIDE GREENS (CI 77288) [] CHROMIUM HYDROXIDE GREEN (CI 77289) [] CARMINE (CI 75470)]

WARNINGS

WARNING: KEEP OUT OF EYES. STOP USE IF IRRITATION OCCURS. KEEP OUT OF REACH OF CHILDREN.

PACKAGE LABEL

ESTEE LAUDER

NUTRITIOUS

VITA-MINERAL LOOSE POWDER

MAKEUP

SPF 15

NT WT 0.52 OZ/15 g

DISTR ESTEE LAUDER INC

NEW YORK, NY 10022